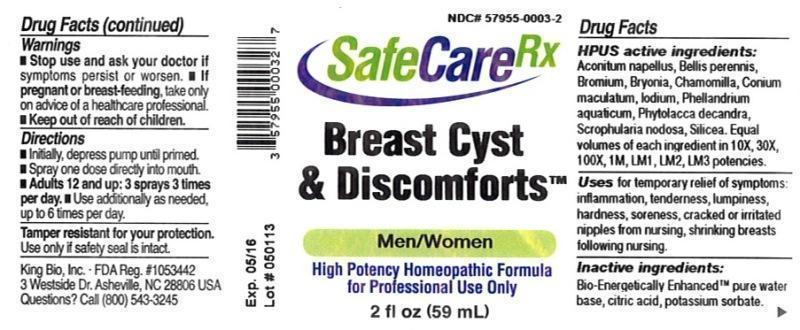 DRUG LABEL: Breast Cyst and Discomforts
NDC: 57955-0003 | Form: LIQUID
Manufacturer: King Bio Inc.
Category: homeopathic | Type: HUMAN OTC DRUG LABEL
Date: 20140417

ACTIVE INGREDIENTS: ACONITUM NAPELLUS 10 [hp_X]/59 mL; BELLIS PERENNIS 10 [hp_X]/59 mL; BROMINE 10 [hp_X]/59 mL; BRYONIA ALBA ROOT 10 [hp_X]/59 mL; MATRICARIA RECUTITA 10 [hp_X]/59 mL; CONIUM MACULATUM FLOWERING TOP 10 [hp_X]/59 mL; IODINE 10 [hp_X]/59 mL; OENANTHE AQUATICA FRUIT 10 [hp_X]/59 mL; PHYTOLACCA AMERICANA ROOT 10 [hp_X]/59 mL; SCROPHULARIA NODOSA 10 [hp_X]/59 mL; SILICON DIOXIDE 10 [hp_X]/59 mL
INACTIVE INGREDIENTS: WATER; CITRIC ACID MONOHYDRATE; POTASSIUM SORBATE

Breast Cyst and Discomforts™

ACTIVE INGREDIENT

Drug Facts__________________________________________________________________________________________________________

HPUS active ingredients: Aconitum napellus, Bellis perennis, Bromium, Bryonia, Chamomilla, Conium maculatum, Iodium, Phellandrium aquaticum, Phytolacca decandra, Scrophularia nodosa, Silicea. Equal volumes of each ingredient in 10X, 30X, 100X, 1M, LM1, LM2, LM3 potencies.

INDICATIONS AND USAGE

Uses for temporary relief of symptoms: inflammation, tenderness, lumpiness, hardness, soreness, cracked or irritated nipples from nursing, shrinking breasts following nursing.

Inactive Ingredients:

Bio-Energetically Enhanced™ pure water, citric acid and potassium sorbate.

Warnings

- Stop use and ask your doctor if symptoms persist or worsen.
- If pregnant or breast-feeding, take only on advice of a healthcare professional.

- Keep out of reach of children.

Directions

- Initially, depress pump until primed.
- Spray one dose directly into mouth.
- Adults: 12 and up: 3 sprays 3 times per day.
- Use additionally as needed, up to 6 times per day.

OTHER SAFETY INFORMATION

Tamper resistant for your protection. Use only if safety seal is intact.

PURPOSE

Uses for temporary relief of symptoms:

- inflammation
- tenderness
- lumpiness
- hardness
- soreness
- cracked or irritated nipples from nursing
- shrinking breasts following nursing